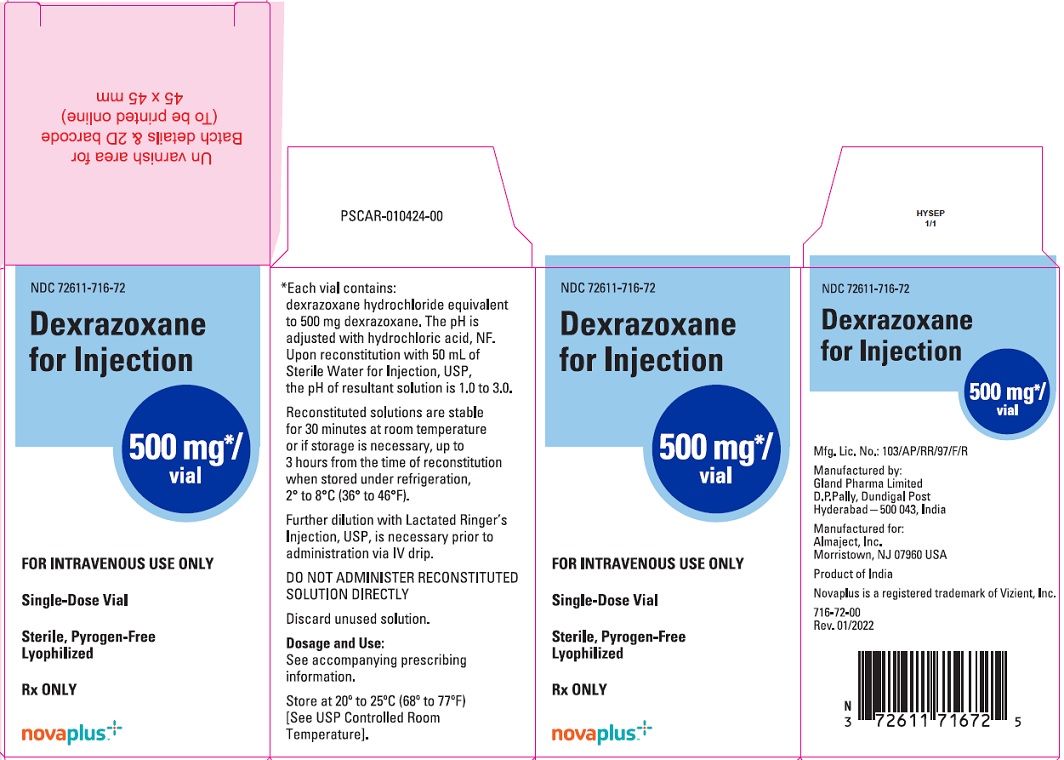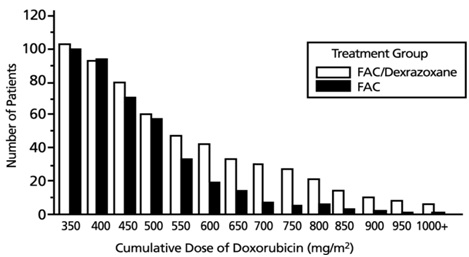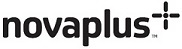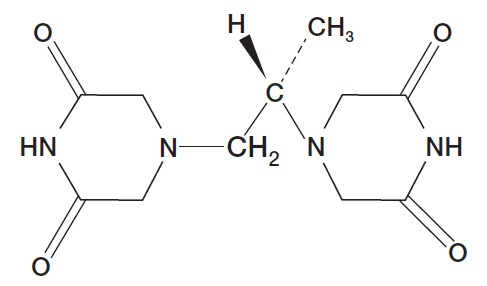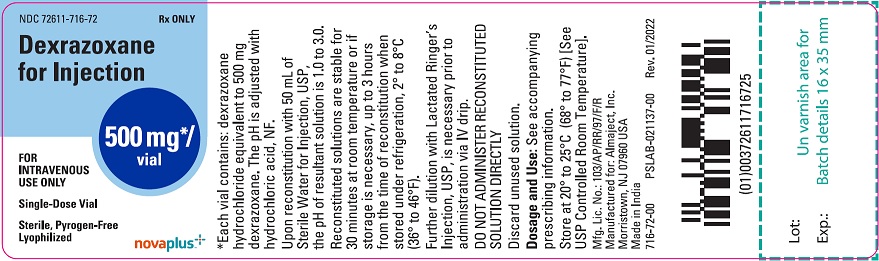 DRUG LABEL: Dexrazoxane
NDC: 72611-716 | Form: INJECTION, POWDER, LYOPHILIZED, FOR SOLUTION
Manufacturer: Almaject, Inc.
Category: prescription | Type: HUMAN PRESCRIPTION DRUG LABEL
Date: 20251209

ACTIVE INGREDIENTS: DEXRAZOXANE HYDROCHLORIDE 500 mg/50 mL
INACTIVE INGREDIENTS: HYDROCHLORIC ACID

HIGHLIGHTS OF PRESCRIBING INFORMATION

These highlights do not include all the information needed to use DEXRAZOXANE FOR INJECTION safely and effectively. See Full Prescribing Information for DEXRAZOXANE FOR INJECTION.
DEXRAZOXANE for injection, for intravenous use
Initial U.S. Approval: 1995

1 INDICATIONS AND USAGE

Dexrazoxane for Injection is a cytoprotective agent indicated for reducing the incidence and severity of cardiomyopathy associated with doxorubicin administration in women with metastatic breast cancer who have received a cumulative doxorubicin dose of 300 mg/m2 and who will continue to receive doxorubicin therapy to maintain tumor control. Do not use Dexrazoxane for Injection with doxorubicin initiation. (1)

2 DOSAGE AND ADMINISTRATION

• Reconstitute vial contents and dilute before use. (2.3)
• Administer Dexrazoxane for Injection by intravenous infusion over 15 minutes.
• DO NOT ADMINISTER VIA AN INTRAVENOUS PUSH. (2.1,2.3)
• The recommended dosage ratio of Dexrazoxane for Injection to doxorubicin is 10:1 (e.g., 500 mg/m^2 Dexrazoxane for Injection to 50 mg/m^2 doxorubicin). Do not administer doxorubicin before Dexrazoxane. (2.1)
• Reduce dose by 50% for patients with creatinine clearance <40 mL/min. (2.2, 8.7)

3 DOSAGE FORMS AND STRENGTHS

500 mg single dose vials as sterile, pyrogen-free lyophilized. (3)

4 CONTRAINDICATIONS

Dexrazoxane for Injection should not be used with non-anthracycline chemotherapy regimens. (4)

5 WARNINGS AND PRECAUTIONS

• Myelosuppression: Dexrazoxane for Injection may increase the myelosuppresive effects of chemotherapeutic agents. Perform hematological monitoring. (5.1)
• Embryo-Fetal Toxicity: Can cause fetal harm. Advise female patients of reproductive potential of the potential hazard to the fetus. (5.5, 8.1)

6 ADVERSE REACTIONS

In clinical studies, Dexrazoxane for Injection was administered to patients also receiving chemotherapeutic agents for cancer. Pain on injection was observed more frequently in patients receiving Dexrazoxane for Injection versus placebo. (6.1)

To report SUSPECTED ADVERSE REACTIONS, contact Almaject, Inc. at 1-866-770-3024 or FDA at 1-800-FDA-1088 or www.fda.gov/medwatch.

8 USE IN SPECIFIC POPULATIONS

• Nursing Mothers: Discontinue drug or nursing. (8.3)

FULL PRESCRIBING INFORMATION

1 INDICATIONS AND USAGE

Dexrazoxane for Injection is indicated for reducing the incidence and severity of cardiomyopathy associated with doxorubicin administration in women with metastatic breast cancer who have received a cumulative doxorubicin dose of 300 mg/m^2 and who will continue to receive doxorubicin therapy to maintain tumor control. Do not use with the initiation of doxorubicin therapy [see Warnings and Precautions (5.2)].

2 DOSAGE AND ADMINISTRATION

2.1 Recommended Dose

Administer Dexrazoxane for Injection via intravenous infusion over 15 minutes. DO NOT ADMINISTER VIA AN INTRAVENOUS PUSH.

The recommended dosage ratio of Dexrazoxane for Injection to doxorubicin is 10:1 (e.g., 500 mg/m^2 Dexrazoxane for Injection to 50 mg/m^2 doxorubicin). Do not administer doxorubicin before Dexrazoxane for Injection. Administer doxorubicin within 30 minutes after the completion of Dexrazoxane for Injection infusion.

2.2 Dose Modifications

Dosing in Patients with Renal Impairment
Reduce Dexrazoxane for Injection dosage in patients with moderate to severe renal impairment (creatinine clearance values less than 40 mL/min) by 50% (Dexrazoxane for Injection to doxorubicin ratio reduced to 5:1; such as 250 mg/m^2 Dexrazoxane for Injection to 50 mg/m^2 doxorubicin) [see Use in Specific Populations (8.6) and Clinical Pharmacology (12.3)].

Dosing in Patients with Hepatic Impairment
Since a doxorubicin dose reduction is recommended in the presence of hyperbilirubinemia, reduce the Dexrazoxane for Injection dosage proportionately (maintaining the 10:1 ratio) in patients with hepatic impairment.

2.3 Preparation and Administration

Preparation and Handling of Infusion Solution
Reconstitute Dexrazoxane for Injection with Sterile Water for Injection, USP. Reconstitute with 50 mL for a Dexrazoxane for Injection 500 mg vial to give a concentration of 10 mg/mL. Dilute the reconstituted solution further with Lactated Ringer's Injection, USP to a concentration of 1.3 to 3.0 mg/mL in intravenous infusion bags for intravenous infusion.

Following reconstitution with Sterile Water for Injection, USP, Dexrazoxane for Injection is stable for 30 minutes at room temperature or if storage is necessary, up to 3 hours from the time of reconstitution when stored under refrigeration, 2° to 8°C (36° to 46°F). The pH of the resultant solution is 1.0 to 3.0. DISCARD UNUSED SOLUTIONS. The diluted infusion solutions are stable for one hour at room temperature or if storage is necessary, up to 4 hours when stored under refrigeration, 2° to 8°C (36° to 46°F). The infusion solutions have a pH of 3.5 to 5.5. DISCARD UNUSED SOLUTIONS.
Parenteral drug products should be inspected visually for particulate matter and discoloration prior to administration, whenever solution and container permit. Solutions containing a precipitate should be discarded.

Use caution when handling and preparing the reconstituted solution. The use of gloves is recommended. If Dexrazoxane for Injection powder or solutions contact the skin or mucosae, wash exposed area immediately and thoroughly with soap and water. Follow special handling and disposal procedures^1.

Administration
Do not mix Dexrazoxane for Injection with other drugs.

Administer the final diluted solution of Dexrazoxane for Injection by intravenous infusion over 15 minutes before the administration of doxorubicin. DO NOT ADMINISTER VIA AN INTRAVENOUS PUSH. Administer doxorubicin within 30 minutes after the completion of Dexrazoxane for Injection infusion.

3 DOSAGE FORMS AND STRENGTHS

Dexrazoxane for Injection is available in 500 mg single dose vials as sterile, pyrogen-free lyophilized.

4 CONTRAINDICATIONS

Do not use Dexrazoxane for Injection with non-anthracycline chemotherapy regimens.

5 WARNINGS AND PRECAUTIONS

5.1 Myelosuppression

Dexrazoxane for Injection may add to the myelosuppression caused by chemotherapeutic agents. Obtain a complete blood count prior to and during each course of therapy, and administer Dexrazoxane for Injection and chemotherapy only when adequate hematologic parameters are met.

5.2 Concomitant Chemotherapy

Only use Dexrazoxane for Injection in those patients who have received a cumulative doxorubicin dose of 300 mg/m^2 and are continuing with doxorubicin therapy. Do not use with chemotherapy initiation as Dexrazoxane for Injection may interfere with the antitumor activity of the chemotherapy regimen. In a trial conducted in patients with metastatic breast cancer who were treated with fluorouracil, doxorubicin, and cyclophosphamide (FAC) with or without Dexrazoxane for Injection starting with their first cycle of FAC therapy, patients who were randomized to receive Dexrazoxane for Injection had a lower response rate (48% vs. 63%) and shorter time to progression than patients who were randomized to receive placebo.

5.3 Cardiac Toxicity

Treatment with Dexrazoxane for Injection does not completely eliminate the risk of anthracycline-induced cardiac toxicity. Monitor cardiac function before and periodically during therapy to assess left ventricular ejection fraction (LVEF). In general, if test results indicate deterioration in cardiac function associated with doxorubicin, the benefit of continued therapy should be carefully evaluated against the risk of producing irreversible cardiac damage.

5.4 Secondary Malignancies

Secondary malignancies such as acute myeloid leukemia (AML) and myelodysplastic syndrome (MDS) have been reported in studies of pediatric patients who have received Dexrazoxane for Injection in combination with chemotherapy. Dexrazoxane for Injection is not indicated for use in pediatric patients. Some adult patients who received Dexrazoxane for Injection in combination with anti-cancer agents known to be carcinogenic have also developed secondary malignancies, including AML and MDS.
Razoxane is the racemic mixture, of which dexrazoxane is the S(+)-enantiomer. Secondary malignancies (primarily acute myeloid leukemia) have been reported in patients treated chronically with oral razoxane. In these patients, the total cumulative dose of razoxane ranged from 26 to 480 grams and the duration of treatment was from 42 to 319 weeks. One case of T-cell lymphoma, one case of B-cell lymphoma, and six to eight cases of cutaneous basal cell or squamous cell carcinoma have also been reported in patients treated with razoxane. Long-term administration of razoxane to rodents was associated with the development of malignancies [see Nonclinical Toxicology (13.1)].

5.5 Embryo-Fetal Toxicity

Dexrazoxane for Injection can cause fetal harm when administered to pregnant women. Dexrazoxane administration during the period of organogenesis resulted in maternal toxicity, embryotoxicity and teratogenicity in rats and rabbits at doses significantly lower than the clinically recommended dose [see Use in Specific Populations (8.1)]. If this drug is used during pregnancy, or if the patient becomes pregnant while taking this drug, the patient should be apprised of the potential hazard to a fetus.
Advise female patients of reproductive potential to avoid becoming pregnant and to use highly effective contraception during treatment [see Use in Specific Populations (8.6)].

6 ADVERSE REACTIONS

6.1 Clinical Trials Experience

Because clinical trials are conducted under widely varying conditions, the adverse reaction rates observed cannot be directly compared to rates in other trials and may not reflect the rates observed in clinical practice.
The adverse reaction profile described in this section was identified from randomized, placebo controlled, double-blind studies in patients with metastatic breast cancer who received the combination of the FAC chemotherapy regimen with or without Dexrazoxane for Injection. The dose of doxorubicin was 50 mg/m^2 in each of these trials. Treatment was administered every three weeks until disease progression or cardiac toxicity.
Patients in clinical trials who received FAC with Dexrazoxane for Injection experienced more severe leukopenia, granulocytopenia, and thrombocytopenia than patients receiving FAC without Dexrazoxane for Injection [see Warnings and Precautions (5.1)].
Table 1 below lists the incidence of adverse reactions for patients receiving FAC with either Dexrazoxane for Injection or placebo in the breast cancer studies. Adverse experiences occurring during courses 1 through 6 are displayed for patients receiving Dexrazoxane for Injection or placebo with FAC beginning with their first course of therapy (columns 1 and 3, respectively). Adverse experiences occurring at course 7 and beyond for patients who received placebo with FAC during the first six courses and who then received either Dexrazoxane for Injection or placebo with FAC are also displayed (columns 2 and 4, respectively).
The adverse reactions listed below in Table 1 demonstrate that the frequency of adverse reaction “Pain on Injection” has been greater for Dexrazoxane for Injection arm, as compared to placebo.

Table 1

Adverse Reaction | Percentage (%) of Breast Cancer Patients With Adverse Reaction
Adverse Reaction | FAC + Dexrazoxane for Injection |  | FAC + Placebo
Adverse Reaction | Courses 1- 6 N = 413 | Courses ≥ 7 N = 102 | Courses 1- 6 N = 458 | Courses ≥ 7 N = 99
Alopecia | 94 | 100 | 97 | 98
Nausea | 77 | 51 | 84 | 60
Vomiting | 59 | 42 | 72 | 49
Fatigue/Malaise | 61 | 48 | 58 | 55
Anorexia | 42 | 27 | 47 | 38
Stomatitis | 34 | 26 | 41 | 28
Fever | 34 | 22 | 29 | 18
Infection | 23 | 19 | 18 | 21
Diarrhea | 21 | 14 | 24 | 7
Pain on Injection | 12 | 13 | 3 | 0
Sepsis | 17 | 12 | 14 | 9
Neurotoxicity | 17 | 10 | 13 | 5
Streaking/Erythema | 5 | 4 | 4 | 2
Phlebitis | 6 | 3 | 3 | 5
Esophagitis | 6 | 3 | 7 | 4
Dysphagia | 8 | 0 | 10 | 5
Hemorrhage | 2 | 3 | 2 | 1
Extravasation | 1 | 3 | 1 | 2
Urticaria | 2 | 2 | 2 | 0
Recall Skin Reaction | 1 | 1 | 2 | 0

7 DRUG INTERACTIONS

No drug interactions have been identified [see Clinical Pharmacology (12.3)].

8 USE IN SPECIFIC POPULATIONS

8.1 Pregnancy

Pregnancy Category D

Risk Summary

Dexrazoxane for Injection can cause fetal harm when administered to pregnant women. Dexrazoxane administration resulted in maternal toxicity, embryotoxicity and teratogenicity in rats and rabbits at doses significantly lower than the clinically recommended dose. If this drug is used during pregnancy, or if the patient becomes pregnant while taking this drug, the patient should be apprised of the potential hazard to a fetus [see Warnings and Precautions (5.5)].

Animal Data

Dexrazoxane resulted in maternal toxicity in rats at doses of ≥2 mg/kg (1/40 the human dose on a mg/m^2 basis) and embryotoxicity and teratogenicity at 8 mg/kg (approximately 1/10 the human dose on a mg/m^2 basis) when given daily to pregnant rats during the period of organogenesis. Teratogenic effects in the rat included imperforate anus, microphthalmia, and anophthalmia. In offspring allowed to develop to maturity, fertility was impaired in the male and female rats treated in utero during organogenesis at 8 mg/kg. In rabbits, doses of ≥5 mg/kg (approximately 1/10 the human dose on a mg/m^2 basis) daily during the period of organogenesis caused maternal toxicity and doses of 20 mg/kg (1/2 the human dose on a mg/m^2 basis) were embryotoxic and teratogenic. Teratogenic effects in the rabbit included several skeletal malformations such as short tail, rib and thoracic malformations, and soft tissue variations including subcutaneous, eye and cardiac hemorrhagic areas, as well as agenesis of the gallbladder and of the intermediate lobe of the lung.

8.3 Nursing Mothers

It is not known whether dexrazoxane or its metabolites are excreted in human milk. Because many drugs are excreted in human milk and because of the potential for serious adverse reactions in nursing infants from dexrazoxane, a decision should be made whether to discontinue nursing or discontinue the drug, taking into account the importance of the drug to the mother.

8.4 Pediatric Use

The safety and effectiveness of dexrazoxane in pediatric patients have not been established [see Warnings and Precautions (5.4)].

8.5 Geriatric Use

Clinical studies of Dexrazoxane for Injection did not include sufficient numbers of subjects aged 65 and over to determine whether they respond differently than younger subjects. Other reported clinical experience has not identified differences in responses between the elderly and younger patients. In general, dose selection for an elderly patient should be cautious, usually starting at the low end of the dosing range, reflecting the greater frequency of decreased hepatic, renal, or cardiac function, and of concomitant disease or other drug therapy.

8.6 Females of Reproductive Potential

Contraception
Dexrazoxane for Injection can cause fetal harm when administered during pregnancy. Advise female patients of reproductive potential to use highly effective contraception during treatment [see Use in Specific Populations (8.1)].

8.7 Renal Impairment

Greater exposure to dexrazoxane may occur in patients with compromised renal function. Reduce the Dexrazoxane for Injection dose by 50% in patients with creatinine clearance values <40 mL/min [see Dosage and Administration (2.2) and Clinical Pharmacology (12.3)].

10 OVERDOSAGE

There are no data on overdosage in the cardioprotective trials; the maximum dose administered during the cardioprotective trials was 1000 mg/m^2 every three weeks.
Disposition studies with Dexrazoxane for Injection have not been conducted in cancer patients undergoing dialysis, but retention of a significant dose fraction (>0.4) of the unchanged drug in the plasma pool, minimal tissue partitioning or binding, and availability of greater than 90% of the systemic drug levels in the unbound form suggest that it could be removed using conventional peritoneal or hemodialysis.
There is no known antidote for dexrazoxane. Instances of suspected overdose should be managed with good supportive care until resolution of myelosuppression and related conditions is complete. Management of overdose should include treatment of infections, fluid regulation, and maintenance of nutritional requirements.

11 DESCRIPTION

Dexrazoxane for injection, a cardioprotective agent for use in conjunction with doxorubicin, is a sterile, pyrogen-free lyophilizate intended for intravenous administration.
Chemically, dexrazoxane is (S)-4,4'-(1-methyl-1,2-ethanediyl)bis-2,6-piperazinedione. The structural formula is as follows:

C11H16N4O4 M.W. 268.28
Dexrazoxane, an intracellular chelating agent, is a derivative of EDTA. Dexrazoxane is a whitish crystalline powder that melts at 191° to 197°C. It is sparingly soluble in water and 0.1 N HCl, slightly soluble in ethanol and methanol, and practically insoluble in nonpolar organic solvents. The pKa is 2.1. Dexrazoxane has an octanol/water partition coefficient of 0.025 and degrades rapidly above a pH of 7.0.
Each 500 mg vial contains dexrazoxane hydrochloride equivalent to 500 mg dexrazoxane. Hydrochloric Acid, NF is added for pH adjustment. When reconstituted as directed with 50 mL of Sterile Water for Injection, USP, each mL contains: 10 mg dexrazoxane. The pH of the resultant solution is 1.0 to 3.0.
The reconstituted Dexrazoxane for Injection solutions prepared from Sterile Water for Injection, USP, are intended for further dilution with Lactated Ringer’s Injection, USP, for rapid intravenous drip infusion. DO NOT ADMINISTER VIA AN INTRAVENOUS PUSH [see Dosage and Administration (2.1, 2.3)].

12 CLINICAL PHARMACOLOGY

12.1 Mechanism of Action

The mechanism by which Dexrazoxane for Injection exerts its cytoprotective activity is not fully understood. Dexrazoxane is a cyclic derivative of EDTA that penetrates cell membranes. Results of laboratory studies suggest that dexrazoxane is converted intracellularly to a ring-opened chelating agent that interferes with iron-mediated free radical generation thought to be responsible, in part, for anthracycline-induced cardiomyopathy.

12.3 Pharmacokinetics

The pharmacokinetics of dexrazoxane have been studied in advanced cancer patients with normal renal and hepatic function. The pharmacokinetics of dexrazoxane can be adequately described by a two-compartment open model with first-order elimination. Dexrazoxane has been administered as a 15 minute infusion over a dose range of 60 to 900 mg/m^2 with 60 mg/m^2 of doxorubicin, and at a fixed dose of 500 mg/m^2 with 50 mg/m^2 doxorubicin. The disposition kinetics of dexrazoxane are dose-independent, as shown by linear relationship between the area under plasma concentration-time curves and administered doses ranging from 60 to 900 mg/m^2. The mean peak plasma concentration of dexrazoxane was 36.5 μg/mL at 15- minute after intravenous administration of 500 mg/m^2 dose of Dexrazoxane for Injection over 15 to 30 minutes prior to the 50 mg/m^2 doxorubicin dose.
The important pharmacokinetic parameters of dexrazoxane are summarized in Table 2:

Table 2: SUMMARY OF MEAN (%CVa) DEXRAZOXANE PHARMACOKINETIC PARAMETERS AT A DOSAGE RATIO OF 10:1 OF DEXRAZOXANE FOR INJECTION: DOXORUBICIN

Dose Doxirubicin (mg/m^2) | Dose Dexrazoxane for Injection (mg/m^2) | Number of Subjects | Elimination Half-Life (h) | Plasma Clearance (L/h/m^2) | Renal Clearance (L/h/m^2) | bVolume of Distribution (L/m^2)
50 60 | 500 600 | 10 5 | 2.5(16) 2.1 (29) | 7.88 (18) 6.25 (31) | 3.35 (36) ------- | 22.4 (22) 22.0 (55)

a Coefficient of variation
b Steady-state volume of distribution
Distribution
Following a rapid distributive phase (0.2 to 0.3 hours), dexrazoxane reaches post-distributive equilibrium within two to four hours. The estimated mean steady-state volume of distribution of dexrazoxane is 22.4 L/m^2 after 500 mg/m^2 of Dexrazoxane for Injection dose followed by 50 mg/m^2 of doxorubicin, suggesting distribution throughout total body water (25 L/m^2).
In vitro studies have shown that dexrazoxane is not bound to plasma proteins.
Metabolism
Qualitative metabolism studies with dexrazoxane have confirmed the presence of unchanged drug, a diacid-diamide cleavage product, and two monoacid-monoamide ring products in the urine of animals and man. The metabolite levels were not measured in the pharmacokinetic studies.
Excretion
Urinary excretion plays an important role in the elimination of dexrazoxane. Forty-two percent of a 500 mg/m^2 dose of Dexrazoxane for Injection was excreted in the urine. Renal clearance averages 3.35 L/h/m^2 after the 500 mg/m^2 Dexrazoxane for Injection dose followed by 50 mg/m^2 of doxorubicin.
Specific Populations
Pediatric
Pharmacokinetics following Dexrazoxane for Injection administration have not been evaluated in pediatric patients.
Effect of Renal Impairment
The pharmacokinetics of dexrazoxane were assessed following a single 15-minute IV infusion of 150 mg/m^2 of Dexrazoxane for Injection. Dexrazoxane clearance was reduced in subjects with renal dysfunction. Compared with controls, the mean AUC0-inf value was two-fold greater in subjects with moderate (CLCR 30-50 mL/min) to severe (CLCR <30 mL/min) renal dysfunction. Modeling demonstrated that equivalent exposure (AUC0-inf) could be achieved if dosing were reduced by 50% in subjects with creatinine clearance values <40 mL/min compared with control subjects (CLCR >80 mL/min) [see Use in Specific Populations (8.7) and Dosage and Administration (2.2)].
Effect of Hepatic Impairment
Pharmacokinetics following Dexrazoxane for Injection administration have not been evaluated in patients with hepatic impairment. The Dexrazoxane for Injection dose is dependent upon the dose of doxorubicin [see Dosage and Administration (2.2)].
Drug Interactions
There was no significant change in the pharmacokinetics of doxorubicin (50 mg/m^2) and its predominant metabolite, doxorubicinol, in the presence of dexrazoxane (500 mg/m^2) in a crossover study in cancer patients.

13 NONCLINICAL TOXICOLOGY

13.1 Carcinogenesis, Mutagenesis, Impairment of Fertility

No long-term carcinogenicity studies have been carried out with dexrazoxane in animals. Nevertheless, a study by the National Cancer Institute has reported that long-term dosing with razoxane (the racemic mixture of dexrazoxane, ICRF-187, and its enantiomer ICRF-186) is associated with the development of malignancies in rats and possibly in mice [see Warnings and Precautions (5.4)].
Dexrazoxane was not mutagenic in the bacterial reverse mutation (Ames) test, but was found to be clastogenic to human lymphocytes in vitro and to mouse bone marrow erythrocytes in vivo (micronucleus test).
Dexrazoxane for Injection has the potential to impair fertility in male patients based on effects in repeat-dose toxicology studies. Testicular atrophy was seen with dexrazoxane administration at doses as low as 30 mg/kg weekly for 6 weeks in rats (1/3 the human dose on a mg/m^2 basis) and as low as 20 mg/kg weekly for 13 weeks in dogs (approximately equal to the human dose on a mg/m^2 basis).

14 CLINICAL STUDIES

The ability of Dexrazoxane for Injection to prevent/reduce the incidence and severity of doxorubicin-induced cardiomyopathy was evaluated in three prospectively randomized placebo-controlled studies. In these studies, patients were treated with a doxorubicin-containing regimen and either Dexrazoxane for Injection or placebo starting with the first course of chemotherapy. There was no restriction on the cumulative dose of doxorubicin. Cardiac function was assessed by measurement of the LVEF, utilizing resting multigated nuclear medicine (MUGA) scans, and by clinical evaluations. Patients receiving Dexrazoxane for Injection had significantly smaller mean decreases from baseline in LVEF and lower incidences of congestive heart failure than the control group; however, in the largest study, patients with advanced breast cancer receiving FAC with Dexrazoxane for Injection had a lower response rate (48% vs. 63%) and a shorter time to progression than patients who received FAC versus placebo.
In the clinical trials, patients who were initially randomized to receive placebo were allowed to receive Dexrazoxane for Injection after a cumulative dose of doxorubicin above 300 mg/m^2. Retrospective historical analyses showed that the risk of experiencing a cardiac event (see Table 3 for definition) at a cumulative dose of doxorubicin above 300 mg/m^2 was greater in the patients who did not receive Dexrazoxane for Injection beginning with their seventh course of FAC than in the patients who did receive Dexrazoxane for Injection (HR=13.08; 95% CI: 3.72, 46.03; p<0.001). Overall, 3% of patients treated with Dexrazoxane for Injection developed CHF compared with 22% of patients not receiving Dexrazoxane for Injection.
Table 3: Definition of Cardiac Events:
1. Development of congestive heart failure, defined as having two or more of the following:
a. Cardiomegaly by X-ray
b. Basilar Rales
c. S3 Gallop
d. Paroxysmal nocturnal dyspnea and/or orthopnea and/or significant dyspnea on exertion.
2. Decline from baseline in LVEF by ≥10% and to below the lower limit of normal for the institution.
3. Decline in LVEF by ≥20% from baseline value.
4. Decline in LVEF to ≥5% below lower limit of normal for the institution.
Figure 1 shows the number of patients still on treatment at increasing cumulative doses.
Figure 1
Cumulative Number of Patients on Treatment FAC vs. FAC/Dexrazoxane for Injection Patients Patients Receiving at Least Seven Courses of Treatment

15 REFERENCES

1. "OSHA Hazardous Drugs." OSHA, http://www.osha.gov/SLTC/hazardousdrugs/index.html

16 HOW SUPPLIED/STORAGE AND HANDLING

Dexrazoxane for injection is available in the following strength as sterile, pyrogen-free lyophilized.
NDC 72611-716-72
500 mg single dose vial with a blue flip-top seal, packaged in single vial packs.
Store at 20° to 25°C (68° to 77°F) [See USP Controlled Room Temperature].
Follow special handling and disposal procedures.^1

17 PATIENT COUNSELING INFORMATION

17.1 Myelosuppression

Treatment with Dexrazoxane for Injection is associated with leukopenia, neutropenia, and thrombocytopenia. Perform hematological monitoring [see Warnings and Precautions (5.1), (5.6)].

17.2 Embryo-Fetal Toxicity

Counsel patients on pregnancy planning and prevention. Advise female patients of reproductive potential that Dexrazoxane for Injection can cause fetal harm and to use highly effective contraception during treatment [see Warnings and Precautions (5.5) and Use in Specific Populations (8.1, 8.6)].

Manufactured by:
Gland Pharma Limited
D.P.Pally, Dundigal Post
Hyderabad - 500 043, India

Manufactured for:
Almaject, Inc.
Morristown, NJ 07960 USA

Product of India

Novaplus is a registered trademark of Vizient, Inc.

Revised: January 2022
PI716-00-NP

Rx only

PRINCIPAL DISPLAY PANEL - vial

NDC 72611-716-72 | Rx ONLY

Dexrazoxane for Injection

500 mg*/vial

FOR INTRAVENOUS USE ONLY

Single-Dose Vial

Sterile, Pyrogen-Free
Lyophilized

*Each vial contains: dexrazoxane hydrochloride equivalent to 500 mg dexrazoxane. The pH is adjusted with hydrochloric acid, NF.

PRINCIPAL DISPLAY PANEL - carton

NDC 72611-716-72

Dexrazoxane for Injection

500 mg*/vial

FOR INTRAVENOUS USE ONLY

Single-Dose Vial

Sterile, Pyrogen-Free
Lyophilized

Rx ONLY

*Each vial contains: dexrazoxane hydrochloride equivalent to 500 mg dexrazoxane. The pH is adjusted with hydrochloric acid, NF.